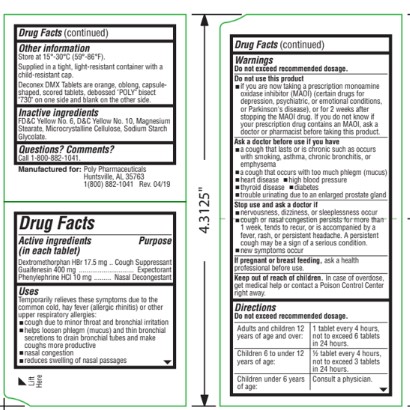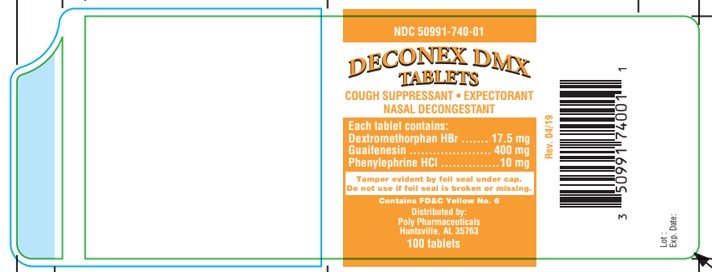 DRUG LABEL: DECONEX
NDC: 50991-740 | Form: TABLET
Manufacturer: Poly Pharmaceuticals, Inc.
Category: otc | Type: HUMAN OTC DRUG LABEL
Date: 20240709

ACTIVE INGREDIENTS: DEXTROMETHORPHAN HYDROBROMIDE 17.5 mg/1 1; GUAIFENESIN 400 mg/1 1; PHENYLEPHRINE HYDROCHLORIDE 10 mg/1 1
INACTIVE INGREDIENTS: SILICON DIOXIDE; CROSCARMELLOSE SODIUM; HYPROMELLOSES; MALTODEXTRIN; POVIDONE; CELLULOSE, MICROCRYSTALLINE; STEARIC ACID

DECONEX DMX TABLETS

Drug Facts

Active ingredients (in each tablet)
Dextromethorphan HBr 17.5 mg
Guaifenesin 400 mg
Phenylephrine HCl 10 mg

Purpose

Cough Suppressant
Expectorant
Nasal Decongestant

Uses

Temporarily relieves these symptoms due to the common cold, hay fever (allergic rhinitis) or other upper respiratory allergies:

- cough due to minor throat and bronchial irritation
- helps loosen phlegm (mucus) and thin bronchial secretions to drain bronchial tubes and make coughs more productive
- nasal congestion
- reduces swelling of nasal passages

Warnings

Do not exceed recommended dosage.

Do not use this product

- if you are now taking a prescription monoamine oxidase inhibitor (MAOI) (certain drugs for depression, psychiatric, or emotional conditions, or Parkinson's disease), or for 2 weeks after stopping the MAOI drug. If you do not know if your prescription drug contains an MAOI, ask a doctor or pharmacist before taking this product.

Ask a doctor before use if you have

- a cough that lasts or is chronic such as occurs with smoking, asthma, chronic bronchitis, or emphysema
- a cough that occurs with too much phlegm (mucus)
- heart disease
- high blood pressure
- thyroid disease
- diabetes
- trouble urinating due to an enlarged prostate gland

Stop use and ask a doctor if

- nervousness, dizziness, or sleeplessness occur
- cough or nasal congestion persists for more than 1 week, tends to recur, or is accompanied by a fever, rash, or persistent headache. A persistent cough may be a sign of a serious condition.
- new symptoms occur

PREGNANCY OR BREAST FEEDING

If pregnant or breast feeding, ask a health professional before use.

Keep out of reach of children. In case of overdose, get medical help or contact a Poison Control Center right away.

Directions

Do not exceed recommended dosage.

Adults and children 12 years of age and over: | 1 tablet every 4 hours, not to exceed 6 tablets in 24 hours
Children 6 to under 12 years of age: | 1/2 tablet every 4 hours, not to exceed 3 tablets in 24 hours
Children under 6 years of age: | Consult a physician.

Other information

Store at 15°- 30° C (59°- 86° F).

Supplied in a tight, light-resistant container with a child-resistant cap.

Deconex DMX Tablets are orange, oblong, capsule-shaped, scored tablets, debossed "POLY" bisect "730" on one side and blank on the other side.

Inactive ingredients

Colloidal Silicon Dioxide, Croscarmellose Sodium, D&C Yellow #10 Aluminum Lake, FD&C Yellow #6 Aluminum Lake, Hypromellose, Maltodextrin, Povidone, Silicified Microcrystalline Cellulose, and Stearic Acid.

Questions? Comments?

Call 1-800-882-1041.

Manufactured for:
Poly Pharmaceuticals
Huntsville, AL
1(800) 882-1041

Rev: 06/19

Product Packaging

The packaging below represents the labeling currently used.

Principal display panel and side panel for 100 tablets label:

NDC 50991-740-01
DECONEX DMX
TABLETS

COUGH SUPPRESSANT · EXPECTORANT
NASAL DECONGESTANT

Each tablet contains:
Dextromethorphan HBr........................17.5 mg
Guaifenesin......................................400 mg
Phenylephrine HCl..............................10 mg

Tamper evident by foil seal under cap.
Do not use if foil seal is broken or missing.

Distributed by:
Poly Pharmaceuticals
Huntsville, AL

100 tablets

Rev. 06-19